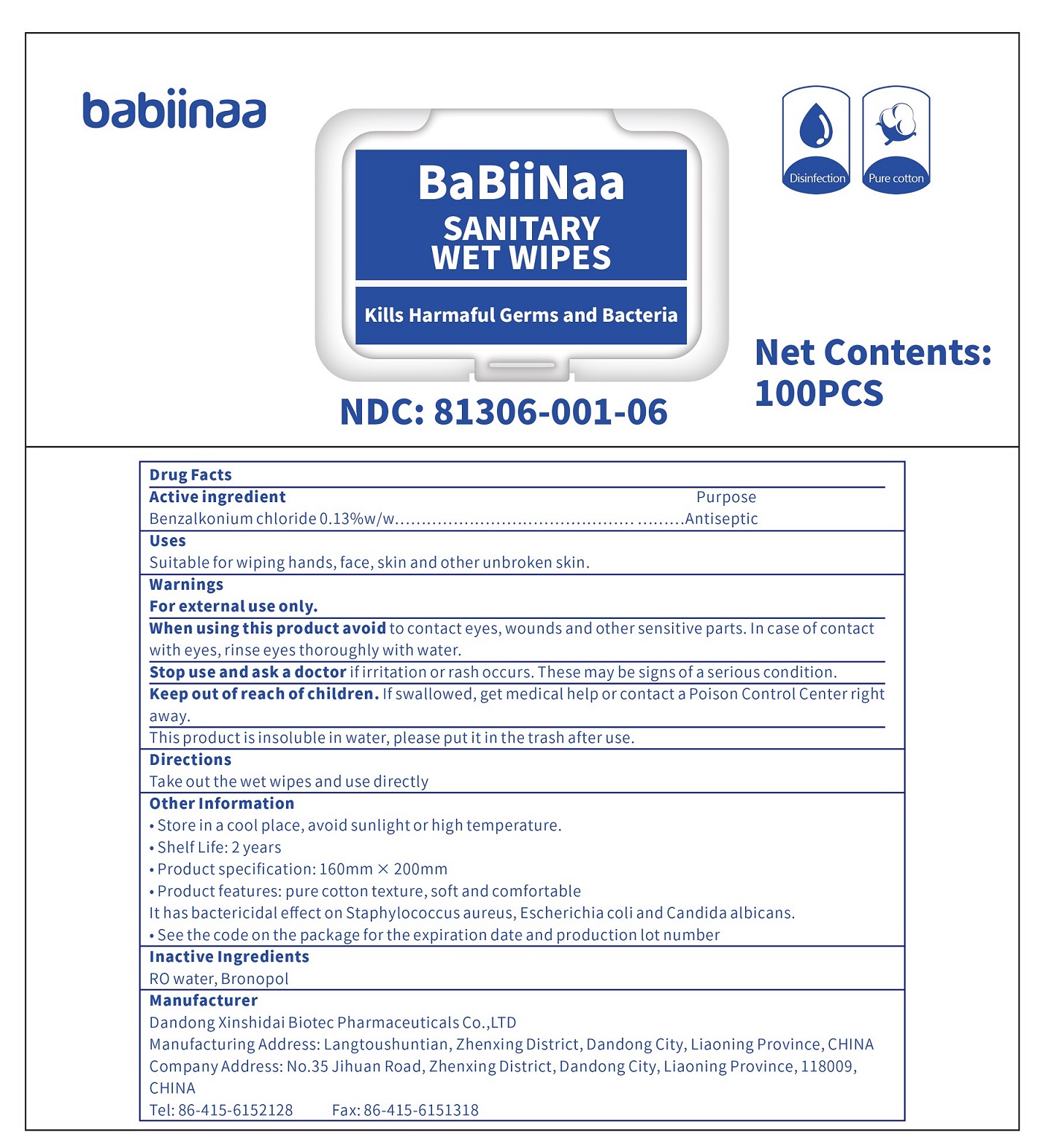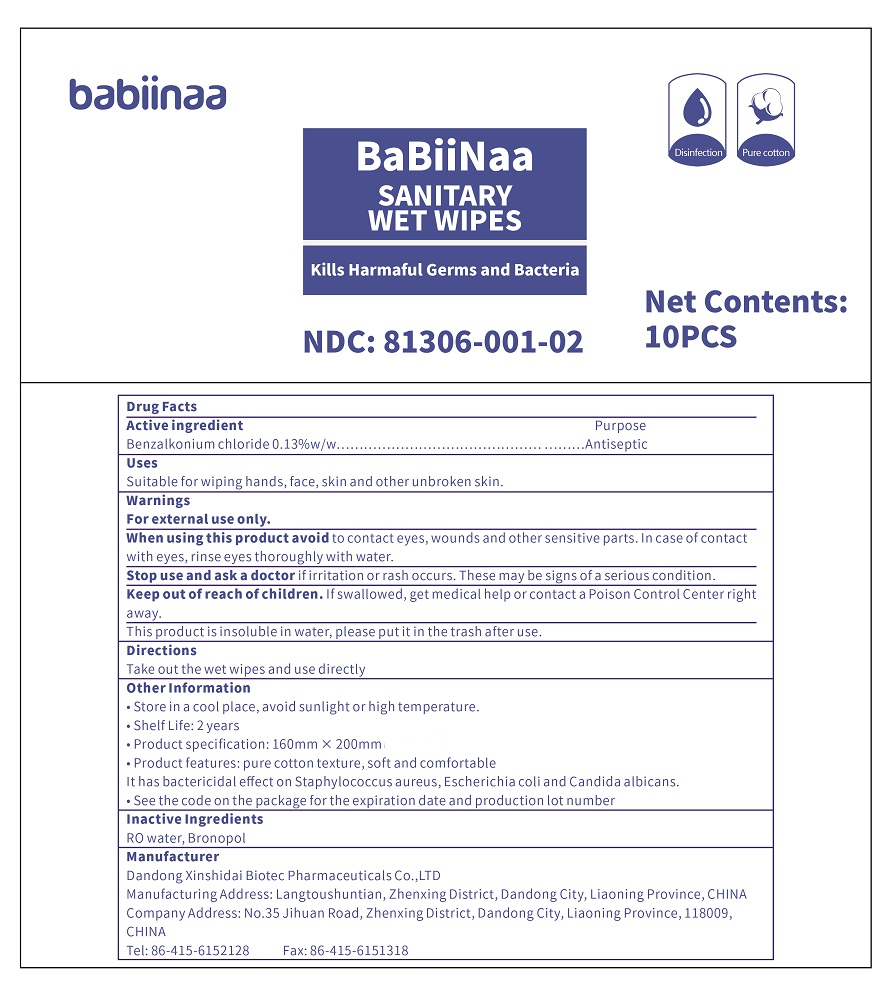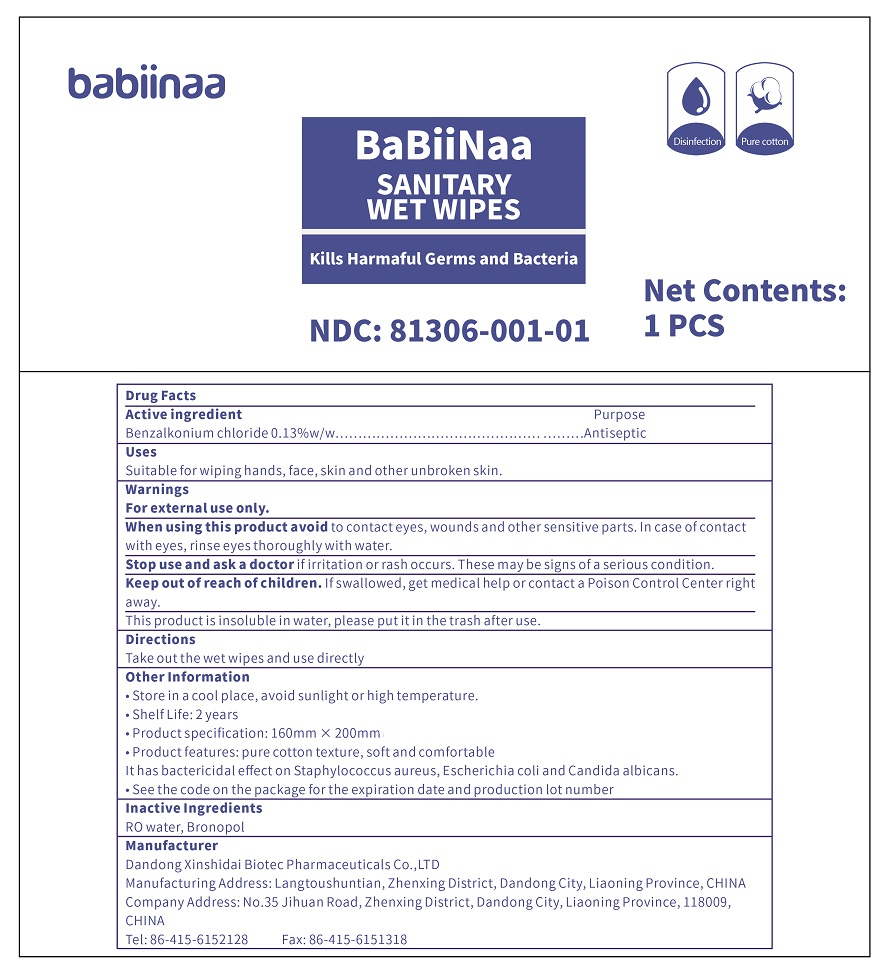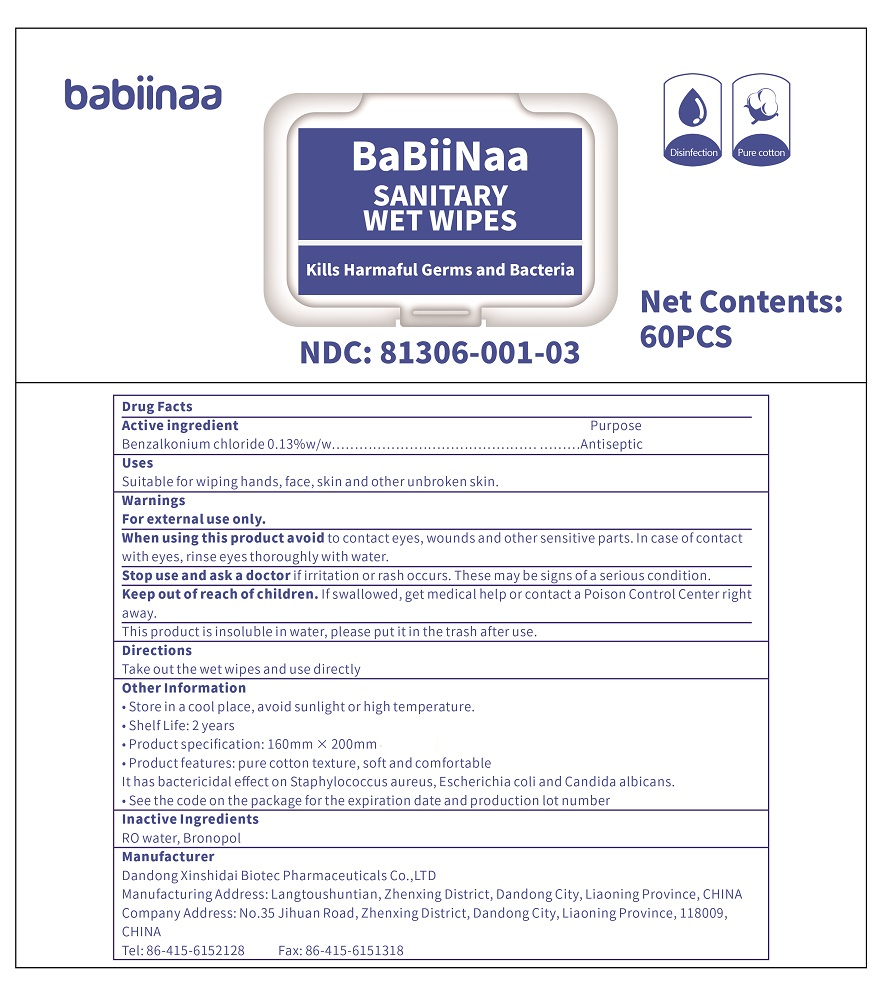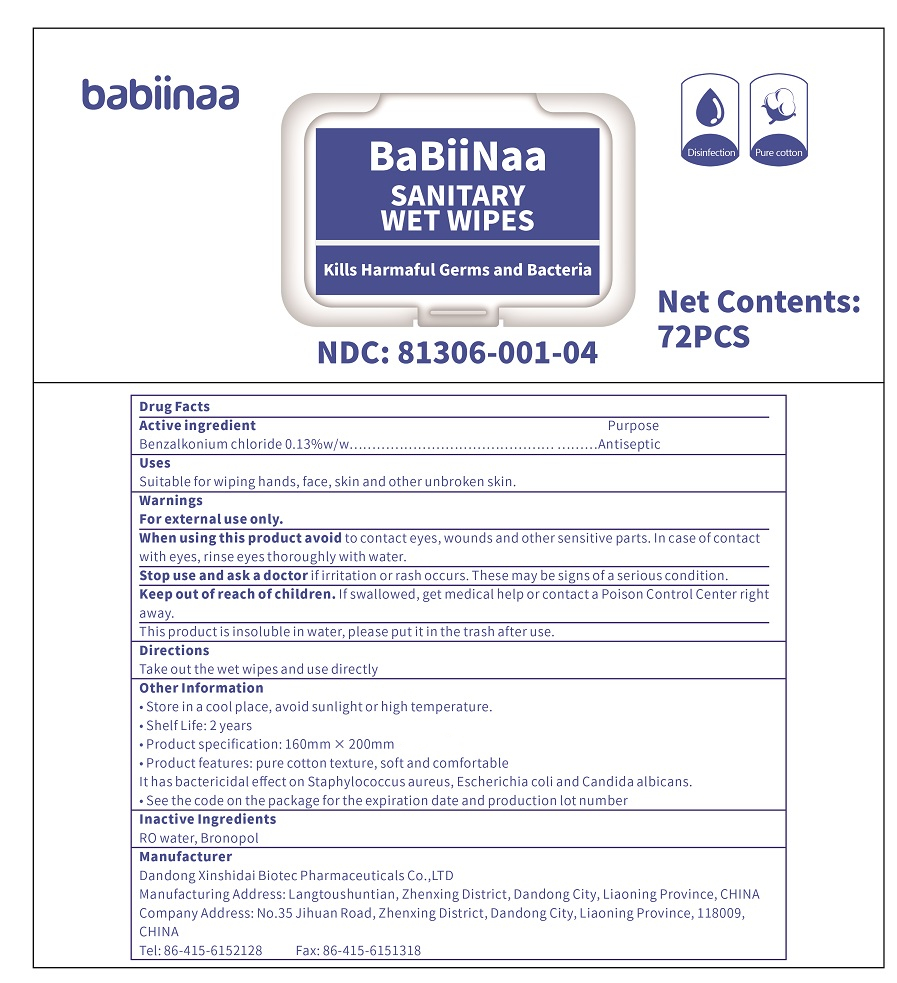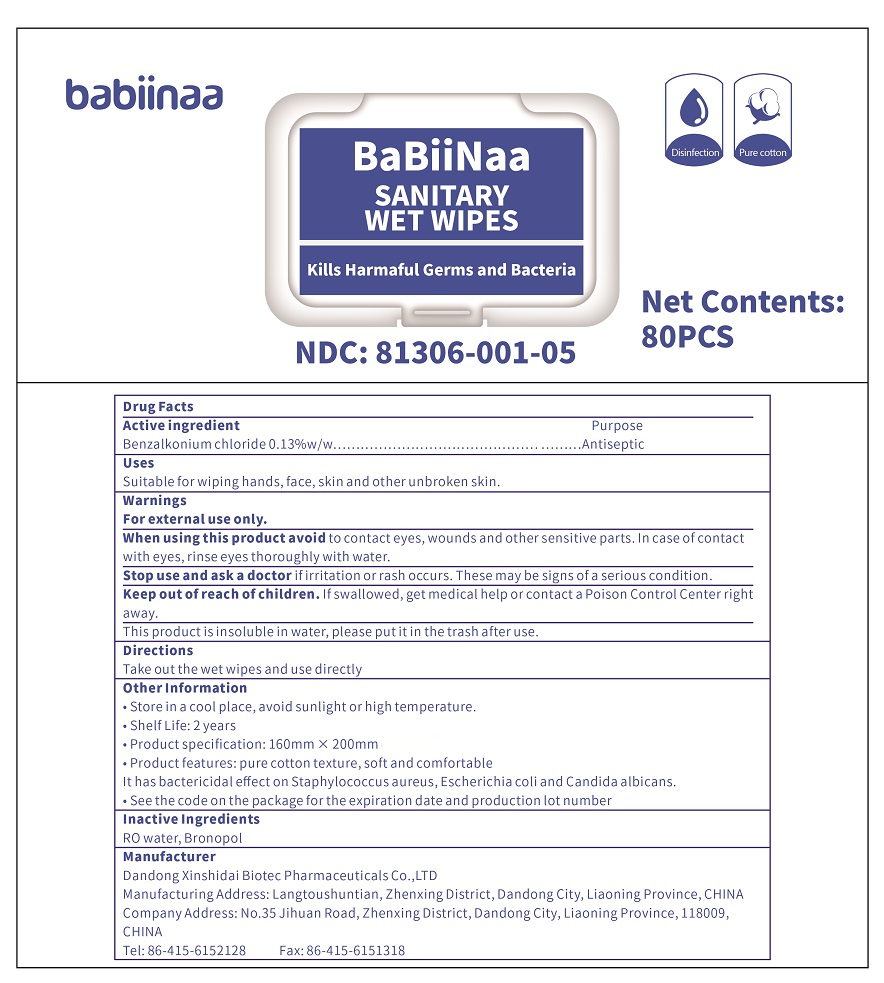 DRUG LABEL: SANITARY WET WIPES
NDC: 81306-001 | Form: CLOTH
Manufacturer: Dandong Xinshidai Biotec Pharmaceuticals Co.,LTD
Category: otc | Type: HUMAN OTC DRUG LABEL
Date: 20201227

ACTIVE INGREDIENTS: BENZALKONIUM CHLORIDE 0.13 g/100 g
INACTIVE INGREDIENTS: WATER; BRONOPOL

SANITARY WET WIPES

Active ingredient

Benzalkonium chloride 0.13% w/w

Purpose

Antiseptic

Uses

Suitable for wiping hands, face, skin and other unbroken skin.

Warnings

For external use only.

When using this product avoid to contact eyes, wounds and other sensitive parts. In case of contact with eyes, rinse eyes thoroughly with water.

Stop use and ask a doctor if irritation or rash occurs. These may be signs of a serious condition.

Keep out of reach of children. If swallowed, get medical help or contact a Poison Control Center right away.

This product is insoluble in water, please put it in the trash after use.

When using this product avoid to contact eyes, wounds and other sensitive parts. In case of contact with eyes, rinse eyes thoroughly with water.

Stop use and ask a doctor if irritation or rash occurs. These may be signs of a serious condition.

Keep out of reach of children. If swallowed, get medical help or contact a Poison Control Center right away.

Directions

Take out the wet wipes and use directly

Other Information

· Store in a cool place, avoid sunlight or high temperature.

· Shelf Life: 2 years

· Product specification: 160mm × 200mm

· Product features: pure cotton texture, soft and comfortable

It has bactericidal effect on Staphylococcus aureus, Escherichia coli and Candida albicans.

· See the code on the package for the expiration date and production lot number

Inactive Ingredients

RO water, Bronopol

PACKAGE LABEL

Net Contents: 1 PCS; NDC: 81306-001-01

Net Contents: 10PCS; NDC: 81306-001-02

Net Contents: 60PCS; NDC: 81306-001-03

Net Contents: 72PCS; NDC: 81306-001-04

Net Contents: 80PCS; NDC: 81306-001-05

Net Contents: 100PCS; NDC: 81306-001-06